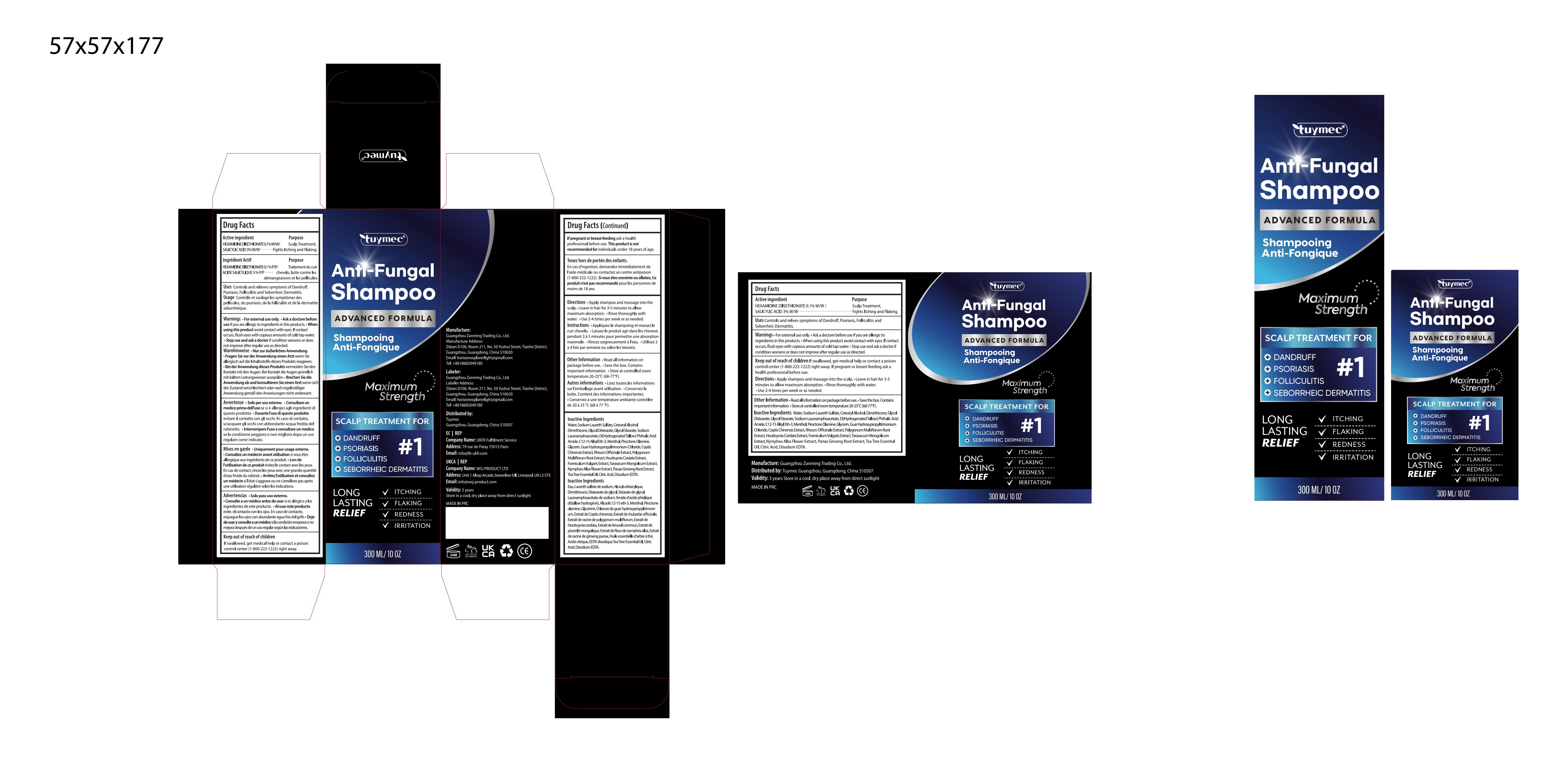 DRUG LABEL: Tuymec Anti-Fungal Shampoo.
NDC: 85150-003 | Form: SHAMPOO
Manufacturer: Guangzhou Zanming Trading Co., Ltd.
Category: otc | Type: HUMAN OTC DRUG LABEL
Date: 20250123

ACTIVE INGREDIENTS: HEXAMIDINE DIISETHIONATE 0.1 g/100 mL; SALICYLIC ACID 3 g/100 mL
INACTIVE INGREDIENTS: FREESIA ALBA FLOWER; TEA TREE OIL; DIMETHICONE; GLYCOL DISTEARATE; COPTIS CHINENSIS ROOT; CITRIC ACID; DIHYDROGENATED TALLOW PHTHALIC ACID AMIDE; PIROCTONE OLAMINE; GUAR HYDROXYPROPYLTRIMONIUM CHLORIDE; HOUTTUYNIA CORDATA FLOWERING TOP; CETOSTEARYL ALCOHOL; WATER; GLYCOL STEARATE; C12-15 ALKYL ETHYLHEXANOATE; MENTHOL; EDETATE DISODIUM; SODIUM LAUROAMPHOACETATE; SODIUM LAURETH SULFATE; RHEUM OFFICINALE ROOT; GLYCERIN; FALLOPIA MULTIFLORA ROOT; ASIAN GINSENG

85150-003

Active Ingredient

HEXAMIDINE DIISETHIONATE 0.1% W/W /
SALICYLIC ACID 3% W/W

Purpose

Scalp treatment,
fights itching and flaking.

Use

Controls and relives symptoms of Dandruff, Psoriasis, Folliculitis and Seborrheic Dermatitis.

Warnings

■ For external use only.
■ Ask a doctore before use if you are allergic to ingredients in this products.
■ When using this product avoid contact with eyes. If contact occurs, flush eyes with copious amounts of cold tap water.
■ Stop use and ask a doctor if condition worsens or does not improve after regular use as directed.

Do not use

If pregnant or breast-feeding ask a health professional before use.
This product is not recommended for individuals under 18 years of age.

When Using

When using this product avoid contact with eyes. If contact occurs, flush eyes with copious amounts of cold tap water.

Stop Use

if condition worsens or does not improve after regular use as directed.

Ask Doctor

If pregnant or breast-feeding ask a health professional before use.

Keep out of reach of children If swallowed, get medical help or contact a poison control center (1-800-222-1222) right away.

Directions

■ Apply shampoo and massage into the scalp.
■ Leave in hair for 3-5 minutes to allow maximum absorption.
■ Rinse thoroughly with water.
■ Use 2-4 times per week or as needed.

Other information

■Read all information on package before use.
■Save the box. Contains important information.
■Store at controlled room temperature 20-25°C (68-77°F).

Inactive ingredients

Water, Sodium Laureth Sulfate, Cetearyl Alcohol, Dimethicone, Glycol Distearate, Glycol Stearate, Sodium Lauroamphoacetate, Di(Hydrogenated Tallow) Phthalic Acid Amide, C12-15 Alkyl Eth-3, Menthol, Piroctone Olamine, Glycerin, Guar Hydroxypropyltrimonium Chloride, Coptis Chinensis Extract, Rheum Officinale Extract, Polygonum Multiflorum Root Extract, Houttuynia Cordata Extract, Foeniculum Vulgaris Extract, Taraxacum Mongolicum Extract, Nymphea Alba Flower Extract, Panax Ginseng Root Extract, Tea Tree Essential Oil, Citric Acid, Disodium EDTA.